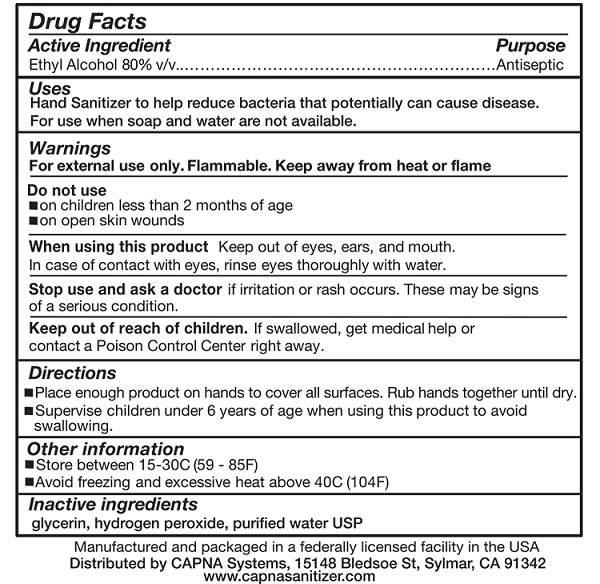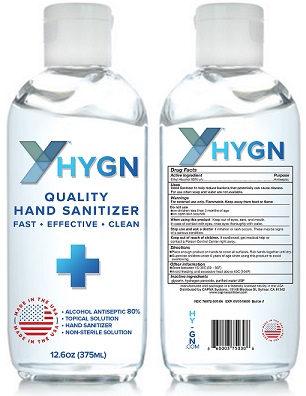 DRUG LABEL: HY-GN Quality Hand and Surface Sanitizers
NDC: 76972-001 | Form: GEL
Manufacturer: TRIFECTA TELECOM HOLDINGS LLC dba HY-GN LLC
Category: otc | Type: HUMAN OTC DRUG LABEL
Date: 20200427

ACTIVE INGREDIENTS: ALCOHOL 80 mL/100 mL
INACTIVE INGREDIENTS: WATER; GLYCERIN; HYDROGEN PEROXIDE

Active Ingredient

Ethyl Alcohol 80% v/v

Purpose

Antiseptic

Uses

Use on hands and surfaces as a disinfecting agents to kill viruses and bacteria

Warnings

For external use only. Flammable. Keep away from heat or flame.

H226 Flammable liquid and vapour.

H319 Causes serious eye irritation.

DO NOT USE on children under the age of 2 months old or open skin wounds

WHEN USING THIS PRODUCT Keep out of eyes, ears and mouth. In case of contact with eyes, rinse thoroughly with water

STOP USE AND ASK A DOCTOR If irritation or rash occur. This may be a sign of a serious condition.

KEEP OUT OF REACH OF CHILDREN If swallowed, seek medical help or contact Poison Control Center right away.

Directions

Place enough product on hands to cover all surfaces. Rub hands together until dry.
Supervise children under 6 years of age when using this product to avoid swallowing.

Other Information:
Store between 15-30C (59-85F)
Avoid Freezing and excessive heat above 40C (104F)

Inactive ingredients

Deionized Water, Glycerin, Hydrogen Peroxide

Package Label - Principal Display Panel

Product label